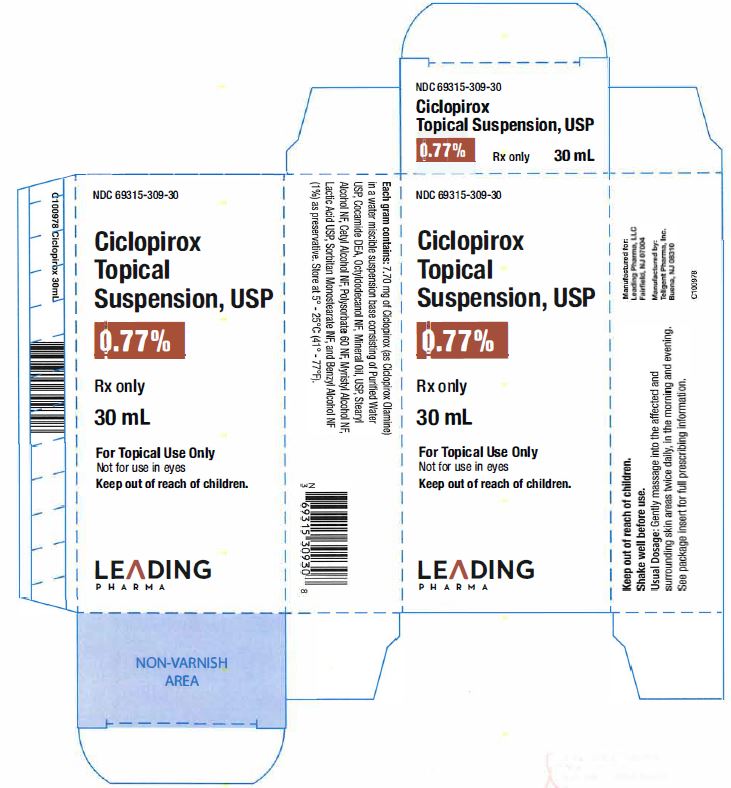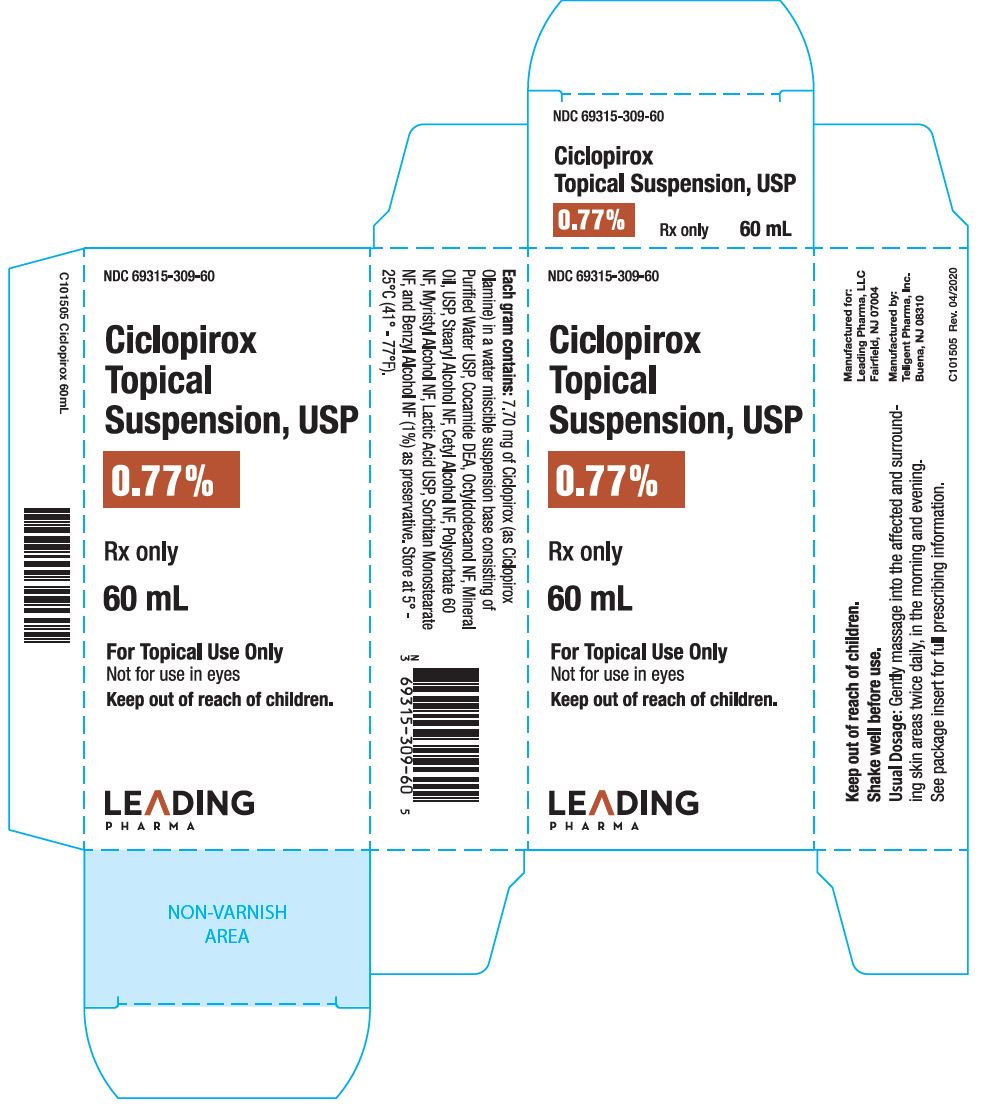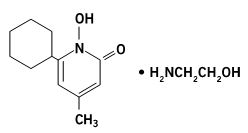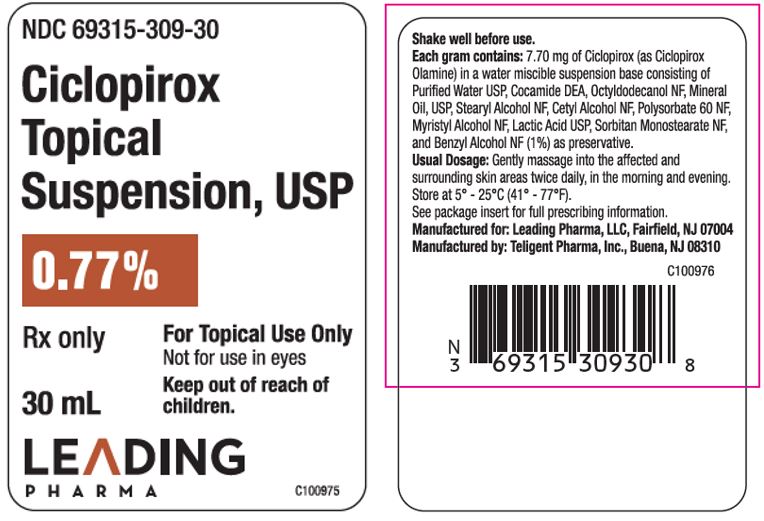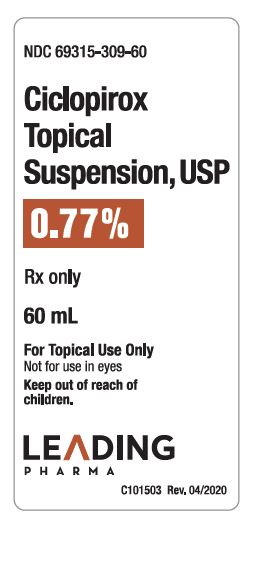 DRUG LABEL: CICLOPIROX OLAMINE
NDC: 69315-309 | Form: SUSPENSION
Manufacturer: Leading Pharma, LLC
Category: prescription | Type: HUMAN PRESCRIPTION DRUG LABEL
Date: 20200430

ACTIVE INGREDIENTS: CICLOPIROX OLAMINE 7.7 mg/1 mL
INACTIVE INGREDIENTS: COCAMIDE; MINERAL OIL; STEARYL ALCOHOL; CETYL ALCOHOL; POLYSORBATE 60; MYRISTYL ALCOHOL; LACTIC ACID; SORBITAN MONOSTEARATE; BENZYL ALCOHOL

Ciclopirox Topical Suspension, USP 0.77%
For Topical Use Only
Not for use in eyes
Rx Only

DESCRIPTION

Ciclopirox Topical Suspension, USP 0.77% is for topical use.

Each ml of Ciclopirox Topical Suspension, USP 0.77% contains 7.70 mg of ciclopirox (as ciclopirox olamine) in a water miscible suspension base consisting of purified water USP, cocamide DEA, octyldodecanol NF, mineral oil USP, stearyl alcohol NF, cetyl alcohol NF, polysorbate 60 NF, myristyl alcohol NF, lactic acid USP, sorbitan monostearate NF, and benzyl alcohol NF (1%) as preservative.

Ciclopirox Topical Suspension, USP 0.77% contains a synthetic, broad spectrum, antifungal agent ciclopirox (as ciclopirox olamine). The chemical name is 6-cyclohexyl-1-hydroxy-4-methyl-2(1H)-pyridone, 2-aminoethanol salt.

The CAS Registry Number is 41621-49-2.

Ciclopirox Topical Suspension, USP 0.77% has a pH of 7.

The chemical structure is:

CLINICAL PHARMACOLOGY

Mechanism of Action

Ciclopirox is a hydroxypyridone antifungal agent that acts by chelation of polyvalent cations (Fe^3+ or Al^3+), resulting in the inhibition of the metal-dependent enzymes that are responsible for the degradation of peroxides within the fungal cell.

Pharmacokinetics

Pharmacokinetic studies in men with radiolabeled ciclopirox solution in polyethylene glycol 400 showed an average of 1.3% absorption of the dose when it was applied topically to 750 cm^2 on the back followed by occlusion for 6 hours. The biological half life was 1.7 hours and excretion occurred via the kidney. Two days after application only 0.01% of the dose applied could be found in the urine. Fecal excretion was negligible. Autoradiographic studies with human cadaver skin showed that ciclopirox penetrates into the hair and through the epidermis and hair follicles into the sebaceous glands and dermis, while a portion of the drug remains in the stratum corneum.

In vitro penetration studies in frozen or fresh excised human cadaver and pig skin indicated that the penetration of Ciclopirox Topical Suspension, USP 0.77% is equivalent to that of Ciclopirox Cream, 0.77%. Therapeutic equivalence of cream and suspension formulations also was indicated by studies of experimentally induced guinea pig and human trichophytosis.

INDICATIONS AND USAGE

Ciclopirox Topical Suspension, USP 0.77% is indicated for the topical treatment of the following dermal infections: tinea pedis, tinea cruris, and tinea corporis due to Trichophyton rubrum, Trichophyton mentagrophytes, Epidermophyton floccosum, and Microsporum canis; ; cutaneous candidiasis (moniliasis) due to Candida albicans; and tinea (pityriasis) versicolor due to Malassezia furfur.

CONTRAINDICATIONS

Ciclopirox Topical Suspension, USP 0.77% is contraindicated in individuals who have shown hypersensitivity to any of its components.

WARNINGS

General

Ciclopirox Topical Suspension, USP 0.77% is not for ophthalmic use.

PRECAUTIONS

If a reaction suggesting sensitivity or chemical irritation should occur with the use of Ciclopirox Topical Suspension, USP 0.77%, treatment should be discontinued and appropriate therapy instituted.

Information for Patients

The patient should be told to:

1. Use the medication for the full treatment time even though signs/symptoms may have improved and notify the physician if there is no improvement after four weeks.
2. Inform the physician if the area of application shows signs of increased irritation (redness, itching, burning, blistering, swelling, oozing) indicative of possible sensitization.
3. Avoid the use of occlusive wrappings or dressings

Carcinogenesis, Mutagenesis, Impairment of Fertility

A 104-week dermal carcinogenicity study in mice was conducted with ciclopirox cream applied at doses up to 1.93% (100 mg/kg/day or 300 mg/m2/day). No increase in drug related neoplasms was noted when compared to control.

The following in vitro genotoxicity tests have been conducted with ciclopirox: evaluation of gene mutation in the Ames Salmonella and E. coli assays (negative); chromosome aberration assays in V79 Chinese hamster lung fibroblast cells, with and without metabolic activation (positive); chromosome aberration assays in V79 Chinese hamster lung fibroblast cells in the presence of supplemental Fe3+, with and without metabolic activation (negative); gene mutation assays in the HGPRT-test with V79 Chinese hamster lung fibroblast cells (negative); and a primary DNA damage assay (i.e., unscheduled DNA synthesis assay in A549 human cells) (negative). An in vitro cell transformation assay in BALB/c 3T3 cells was negative for cell transformation. In an in vivo Chinese hamster bone marrow cytogenetic assay, ciclopirox was negative for chromosome aberrations at a dosage of 5000 mg/kg body weight.

A combined oral fertility and embryofetal developmental study was conducted in rats with ciclopirox olamine. No effect on fertility or reproductive performance was noted at the highest dose tested of 3.85 mg/kg/day ciclopirox (approximately 1.2 times the maximum recommended human dose based on body surface area comparisons).

Pregnancy

Teratogenic Effects: Pregnancy Category B

There are no adequate or well-controlled studies in pregnant women. Therefore, Ciclopirox Topical Suspension, USP 0.77% should be used during pregnancy only if the potential benefit justifies the potential risk to the fetus.

Oral embryofetal developmental studies were conducted in mice, rats, rabbits and monkeys. Ciclopirox or ciclopirox olamine was orally administered during the period of organogenesis. No maternal toxicity, embryotoxicity or teratogenicity were noted at the highest doses of 77, 125, 80 and 38.5 mg/kg/day ciclopirox in mice, rats, rabbits and monkeys, respectively (approximately 11, 37, 51 and 24 times the maximum recommended human dose based on body surface area comparisons, respectively).

Dermal embryofetal developmental studies were conducted in rats and rabbits with ciclopirox olamine dissolved in PEG 400. Ciclopirox olamine was topically administered during the period of organogenesis. No maternal toxicity, embryotoxicity or teratogenicity were noted at the highest doses of 92 mg/kg/day and 77 mg/kg/day ciclopirox in rats and rabbits, respectively (approximately 27 and 49 times the maximum recommended human dose based on body surface area comparisons, respectively).

Nursing Mothers

It is not known whether this drug is excreted in human milk. Caution should be exercised when Ciclopirox Topical Suspension, USP 0.77% is administered to a nursing woman.

Pediatric Use

Safety and effectiveness in pediatric patients below the age of 10 years have not been established.

ADVERSE REACTIONS

In the controlled clinical trial with 89 patients using Ciclopirox Topical Suspension, USP 0.77% and 89 patients using the vehicle, the incidence of adverse reactions was low. Those considered possibly related to treatment or occurring in more than one patient were pruritus, which occurred in two patients using ciclopirox suspension and one patient using the suspension vehicle, and burning, which occurred in one patient using ciclopirox suspension.

DOSAGE AND ADMINISTRATION

Gently massage Ciclopirox Topical Suspension, USP 0.77% into the affected and surrounding skin areas twice daily, in the morning and evening. Clinical improvement with relief of pruritus and other symptoms usually occurs within the first week of treatment. If a patient shows no clinical improvement after four weeks of treatment with Ciclopirox Topical Suspension, USP 0.77%, the diagnosis should be redetermined. Patients with tinea versicolor usually exhibit clinical and mycological clearing after two weeks of treatment.

HOW SUPPLIED

Ciclopirox Topical Suspension, USP 0.77% is supplied in

30 mL bottles (NDC 69315-309-30)
60 mL bottles (NDC 69315-309-60)

Bottle space provided to allow for vigorous shaking before each use.

Store between 5º - 25ºC (41º - 77ºF).

To report SUSPECTED ADVERSE REACTIONS, call 1-866-306-4256 or FDA at 1-800-FDA-1088 or www.fda.gov/medwatch.

Manufactured for: Leading Pharma, LLC

3 Oak Road, Fairfield, NJ 07004-2402 USA

www.leadingpharma.com

Manufactured by: Teligent Pharma, Inc., Buena, NJ 08310

Iss. 09/18